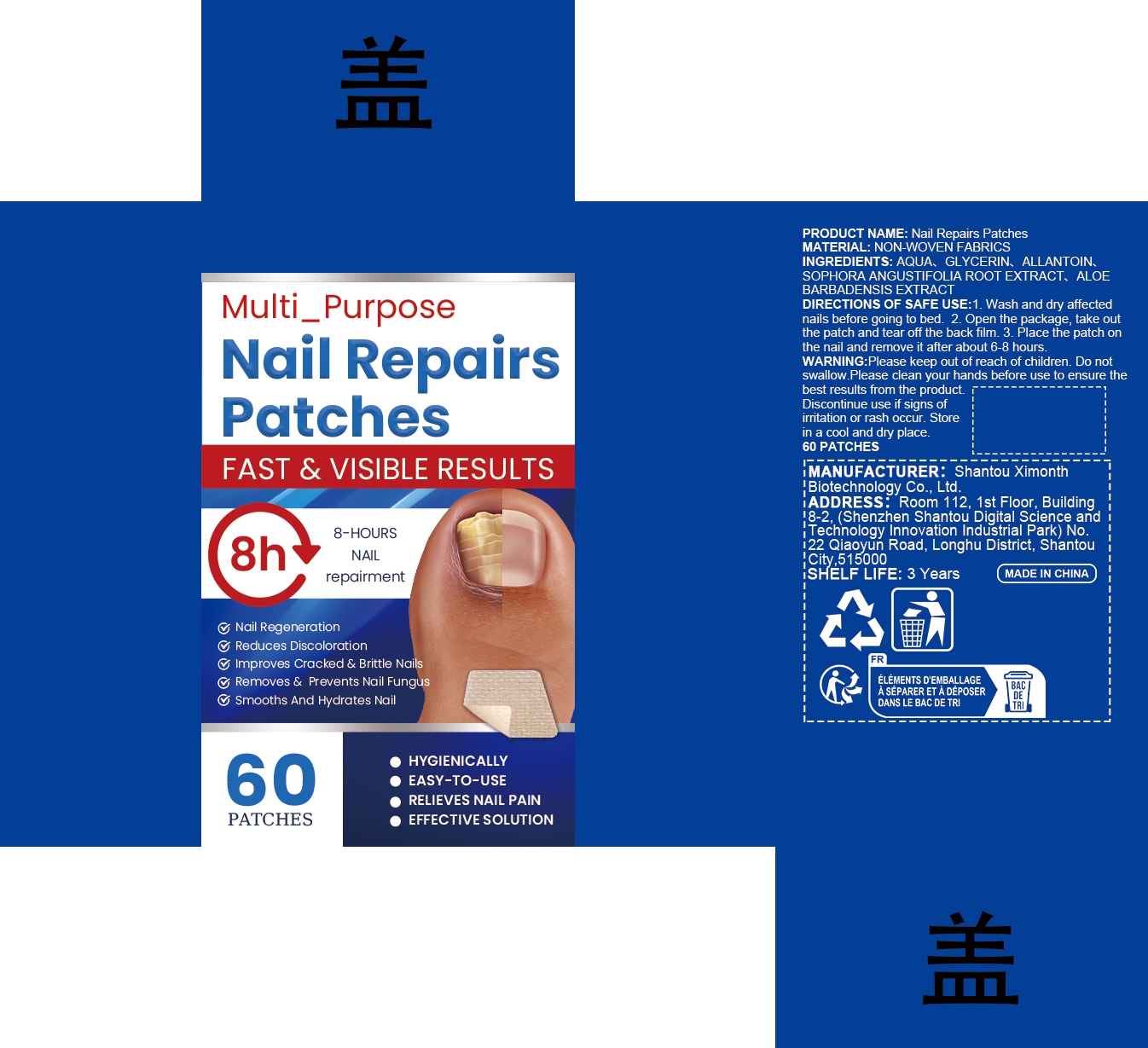 DRUG LABEL: Nail Repairs Patches
NDC: 84989-016 | Form: PATCH
Manufacturer: Shantou Ximonth Biotechnology Co., Ltd.
Category: otc | Type: HUMAN OTC DRUG LABEL
Date: 20260116

ACTIVE INGREDIENTS: ALOE BARBADENSIS LEAF 0.012 mg/60 mg; SOPHORA FLAVESCENS ROOT 0.012 mg/60 mg
INACTIVE INGREDIENTS: ALLANTOIN 0.06 mg/60 mg; GLYCERIN 3 mg/60 mg; AQUA 56.916 mg/60 mg

ACTIVE INGREDIENT

SOPHORA ANGUSTIFOLIA ROOT EXTRACT、ALOE BARBADENSIS EXTRACT

PURPOSE

1. A variety of moisturizing ingredients are absorbed into nails and skin through the patch, deeply nourishing, hydrating brittle nails, and reducing the appearance of thick and discolored nails.

2. Replenish nails with necessary moisture and nutrients, quickly reduce brittle manicure overnight, and restore manicure to show its natural, healthy appearance.

3. Hygienic material support, soft and strong, can provide gentle repair to nails.

4. The packaging is compact and easy to use. The patch design is suitable for carrying when going out and can be used anytime and anywhere.

WHEN USING

1. Wash and dry affected nails before going to bed
2. Open the package, take out the patch and tear off the back film
3. Place the patch on the nail and remove it after about 6-8 hours

Keep out of reach of children.Avoid contact with eyes.Discontinue use if signs of irritation or rash occur.Store in a cool and dry place.

DO NOT USE

Discontinue use if signs of irritation or rash occur.

STOP USE

Discontinue use if signs of irritation or rash occur.

Keep out of reach of children.

STORAGE AND HANDLING

Store in a cool and dry place.

INACTIVE INGREDIENT

AQUA、GLYCERIN、ALLANTOIN

INDICATIONS AND USAGE

1. Wash and dry affected nails before going to bed

2. Open the package, take out the patch and tear off the back film

3. Place the patch on the nail and remove it after about 6-8 hours

DOSAGE AND ADMINISTRATION

1. Wash and dry affected nails before going to bed

2. Open the package, take out the patch and tear off the back film

3. Place the patch on the nail and remove it after about 6-8 hours